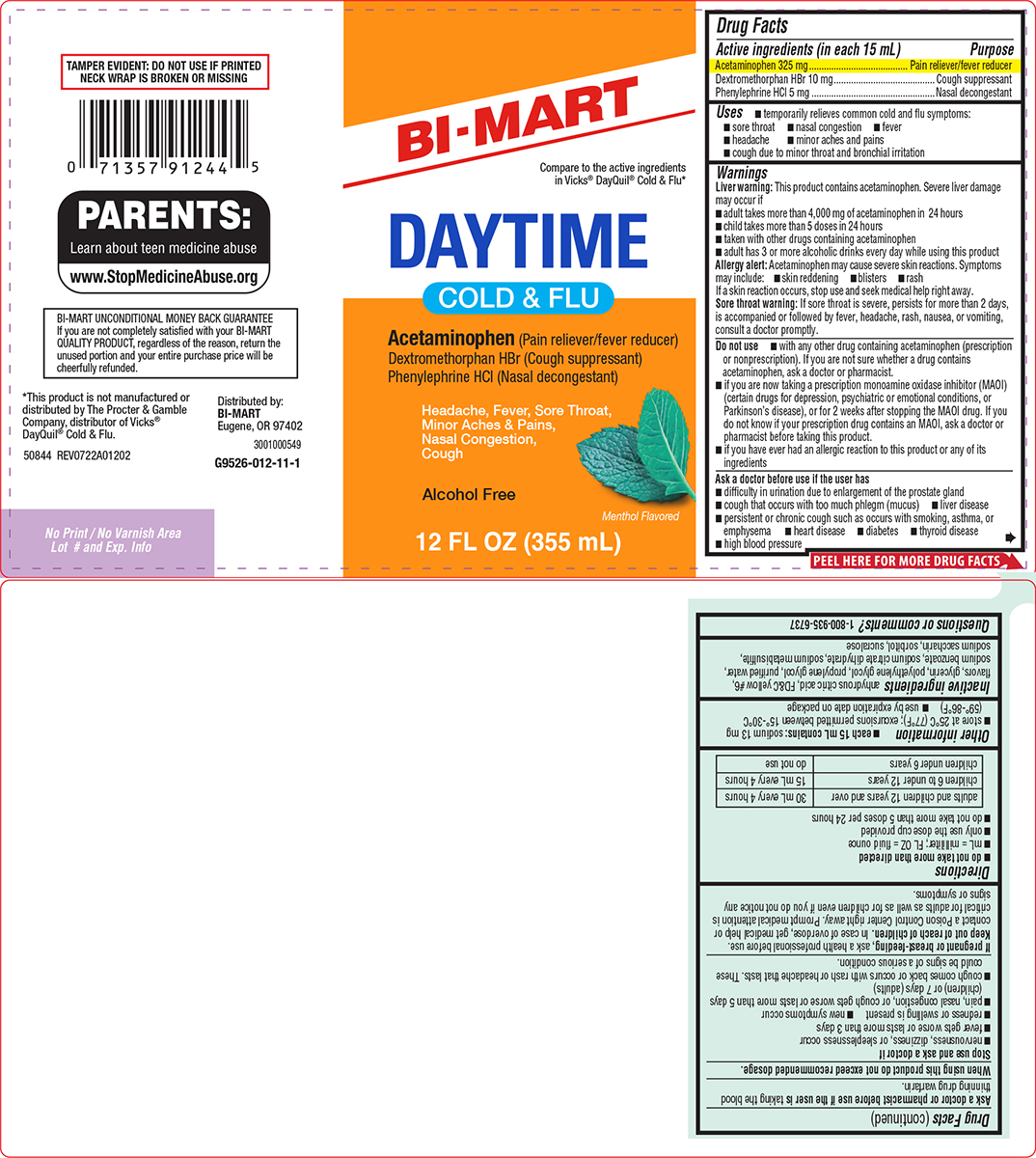 DRUG LABEL: Cold and Flu
NDC: 37835-526 | Form: SOLUTION
Manufacturer: Bi-Mart
Category: otc | Type: HUMAN OTC DRUG LABEL
Date: 20260102

ACTIVE INGREDIENTS: ACETAMINOPHEN 325 mg/15 mL; DEXTROMETHORPHAN HYDROBROMIDE 10 mg/15 mL; PHENYLEPHRINE HYDROCHLORIDE 5 mg/15 mL
INACTIVE INGREDIENTS: ANHYDROUS CITRIC ACID; FD&C YELLOW NO. 6; GLYCERIN; POLYETHYLENE GLYCOL, UNSPECIFIED; PROPYLENE GLYCOL; WATER; SODIUM BENZOATE; TRISODIUM CITRATE DIHYDRATE; SODIUM METABISULFITE; SACCHARIN SODIUM; SORBITOL; SUCRALOSE

Bi-Mart 44-012

Active ingredients (in each 15 mL)

Acetaminophen 325 mg
Dextromethorphan HBr 10 mg
Phenylephrine HCl 5 mg

Purpose

Pain reliever/fever reducer
Cough suppressant
Nasal decongestant

Uses

- temporarily relieves common cold and flu symptoms:
  - sore throat
  - nasal congestion
  - fever
  - headache
  - minor aches and pains
  - cough due to minor throat and bronchial irritation

Warnings

Liver warning: This product contains acetaminophen. Severe liver damage may occur if

- adult takes more than 4,000 mg of acetaminophen in 24 hours
- child takes more than 5 doses in 24 hours
- taken with other drugs containing acetaminophen
- adult has 3 or more alcoholic drinks every day while using this product

Allergy alert: Acetaminophen may cause severe skin reactions. Symptoms may include:

- skin reddening
- blisters
- rash

If a skin reaction occurs, stop use and seek medical help right away.

Sore throat warning: If sore throat is severe, persists for more than 2 days, is accompanied or followed by fever, headache, rash, nausea, or vomiting, consult a doctor promptly.

Do not use

- with any other drug containing acetaminophen (prescription or nonprescription). If you are not sure whether a drug contains acetaminophen, ask a doctor or pharmacist.
- if you are now taking a prescription monoamine oxidase inhibitor (MAOI) (certain drugs for depression, psychiatric or emotional conditions, or Parkinson’s disease), or for 2 weeks after stopping the MAOI drug. If you do not know if your prescription drug contains an MAOI, ask a doctor or pharmacist before taking this product.
- if you have ever had an allergic reaction to this product or any of its ingredients

Ask a doctor before use if the user has

- difficulty in urination due to enlargement of the prostate gland
- cough that occurs with too much phlegm (mucus)
- liver disease
- persistent or chronic cough such as occurs with smoking, asthma, or emphysema
- heart disease
- diabetes
- thyroid disease
- high blood pressure

Ask a doctor or pharmacist before use if the user is

taking the blood thinning drug warfarin.

When using this product

do not exceed recommended dosage.

Stop use and ask a doctor if

- nervousness, dizziness, or sleeplessness occur
- fever gets worse or lasts more than 3 days
- redness or swelling is present
- new symptoms occur
- pain, nasal congestion, or cough gets worse or lasts more than 5 days (children) or 7 days (adults)
- cough comes back or occurs with rash or headache that lasts. These could be signs of a serious condition.

If pregnant or breast-feeding,

ask a health professional before use.

Keep out of reach of children.

In case of overdose, get medical help or contact a Poison Control Center right away. Prompt medical attention is critical for adults as well as for children even if you do not notice any signs or symptoms.

Directions

- do not take more than directed
- mL = milliliter; FL OZ = fluid ounce
- only use the dose cup provided
- do not take more than 5 doses per 24 hours

adults and children 12 years and over | 30 mL every 4 hours
children 6 to under 12 years | 15 mL every 4 hours
children under 6 years | do not use

Other information

- each 15 mL contains: sodium 13 mg
- store at 25°C (77°F); excursions permitted between 15°-30°C (59°-86°F)
- use by expiration date on package

Inactive ingredients

anhydrous citric acid, FD&C yellow #6, flavors, glycerin, polyethylene glycol, propylene glycol, purified water, sodium benzoate, sodium citrate dihydrate, sodium metabisulfite, sodium saccharin, sorbitol, sucralose

Questions or comments?

1-800-935-6737

Principal display panel

BI-MART

Compare to the active ingredients
in Vicks® DayQuil® Cold & Flu*

DAYTIME
COLD & FLU

Acetaminophen (Pain reliever/fever reducer)
Dextromethorphan HBr (Cough suppressant)
Phenylephrine HCl (Nasal decongestant)

Headache, Fever, Sore Throat,
Minor Aches & Pains,
Nasal Congestion,
Cough

Alcohol Free

Menthol Flavored

12 FL OZ (355 mL)

TAMPER EVIDENT: DO NOT USE IF PRINTED
NECK WRAP IS BROKEN OR MISSING

PARENTS:
Learn about teen medicine abuse
www.StopMedicineAbuse.org

BI-MART UNCONDITIONAL MONEY BACK GUARANTEE
If you are not completely satisfied with your BI-MART
QUALITY PRODUCT, regardless of the reason, return the
unused portion and your entire purchase price will be
cheerfully refunded.

*This product is not manufactured or
distributed by The Procter & Gamble
Company, distributor of Vicks®
DayQuil® Cold & Flu.

50844 REV0722A01202

Distributed by:
BI-MART
Eugene, OR 97402

Bi-Mart 44-012